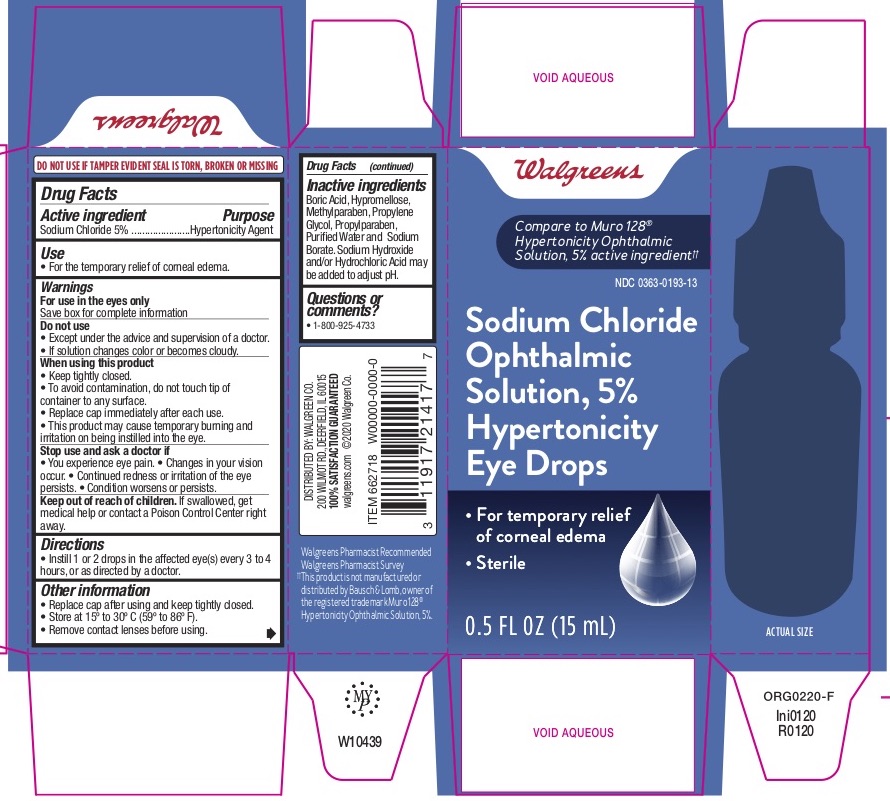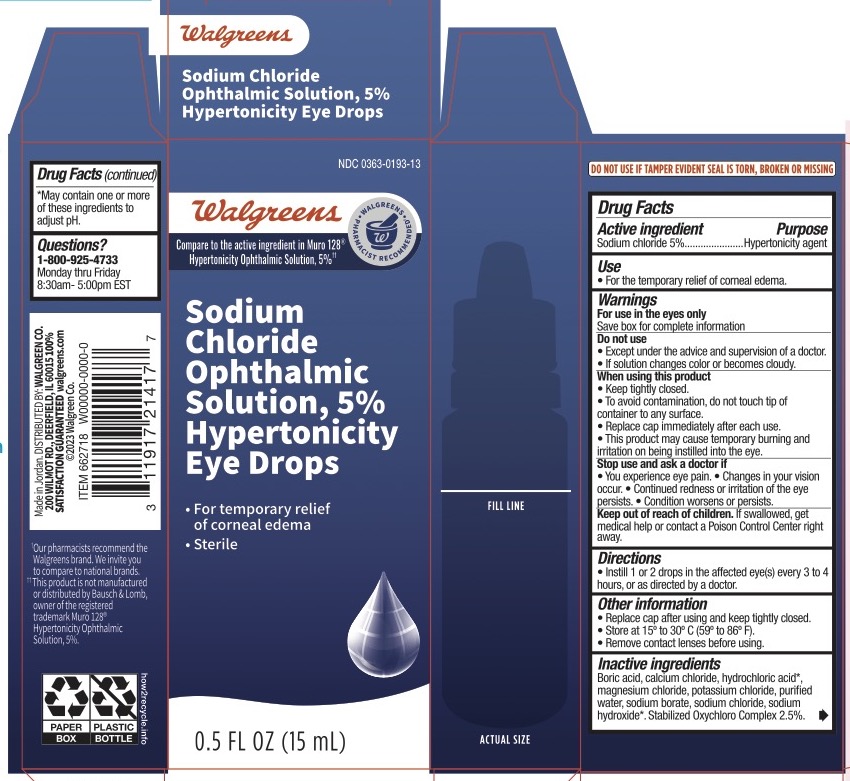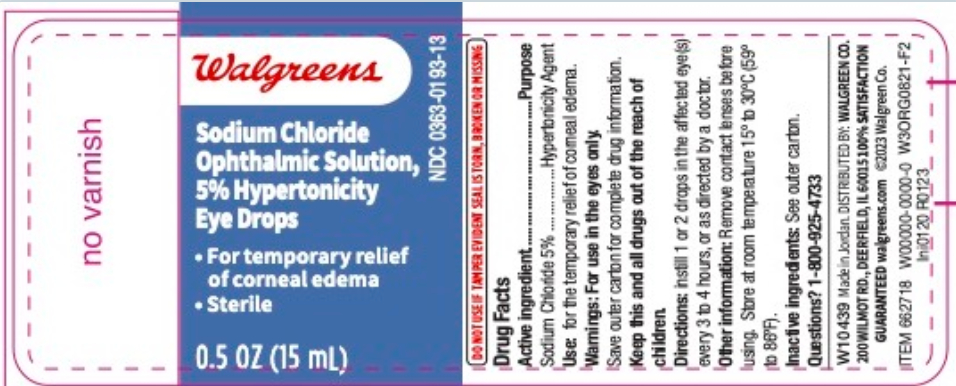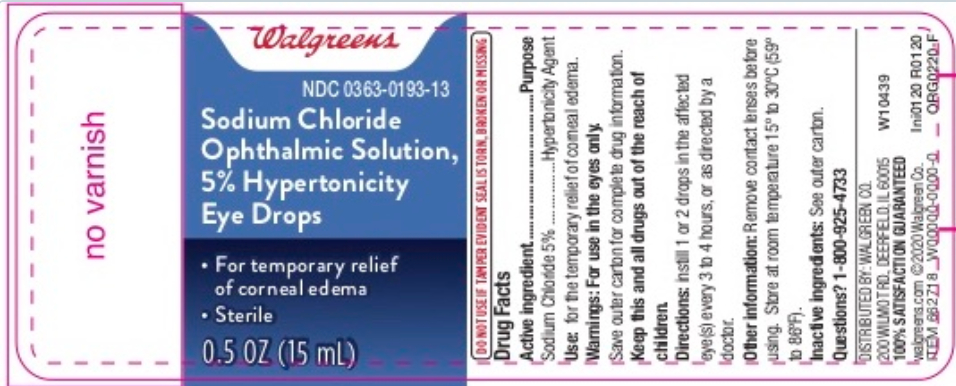 DRUG LABEL: Sodium Chloride
NDC: 0363-0193 | Form: SOLUTION/ DROPS
Manufacturer: Walgreen Company
Category: otc | Type: HUMAN OTC DRUG LABEL
Date: 20251119

ACTIVE INGREDIENTS: SODIUM CHLORIDE 50 mg/1 mL
INACTIVE INGREDIENTS: BORIC ACID; HYPROMELLOSE, UNSPECIFIED; METHYLPARABEN; PROPYLENE GLYCOL; PROPYLPARABEN; SODIUM BORATE; WATER; SODIUM HYDROXIDE; HYDROCHLORIC ACID

Walgreens Sodium Chloride Ophthalmic Solution

Walgreen’s Sodium Chloride Ophthalmic

Solution, 5% Hypertonicity Eye Drops 15mL

NDC 0363-0193-13

Drug Facts

Active ingredient

Sodium Chloride 5%

Purpose

Hypertonicity Agent

Use

• For the temporary relief of corneal edema.

Warnings

For use in the eyes only

Save box for complete information

Do not use

• except under the advice and supervision of a doctor.

• if solution changes color or becomes cloudy.

When using this product

• keep tightly closed.

• to avoid contamination, do not touch tip of container to any surface.

• replace cap immediately after each use.

• this product may cause temporary burning and irritation on being instilled into the eye.

Stop use and ask a doctor if

• you experience eye pain. • changes in your vision occur.

• continued redness or irritation of the eye persists.

• condition worsens or persists.

Keep out of reach of children.

If swallowed, get medical help or contact a Poison Control Center right away.

Directions

• instill 1 or 2 drops in the affected eye(s) every 3 to 4 hours, or as directed by a doctor.

Other information

• replace cap after using and keep tightly closed.

• store at 15° to 30°C (59° to 86°F).

• remove contact lenses before using.

Inactive ingredients

Boric Acid, Hypromellose, Methylparaben, Propylene Glycol, Propylparaben, Sodium Borate, and Water for injection. Sodium Hydroxide and/or Hydrochloric Acid may be added to adjust pH.

Questions?

• 1-800-925-4733 • 9am – 5pm EST Monday - Friday

PRINCIPAL DISPLAY PANEL

Walgreens
NDC 0363-0193-13
Sodium Chloride
Ophthalmic
Solution, 5%
Hypertonicity
Eye Drops
0.5 FL OZ (15 mL)